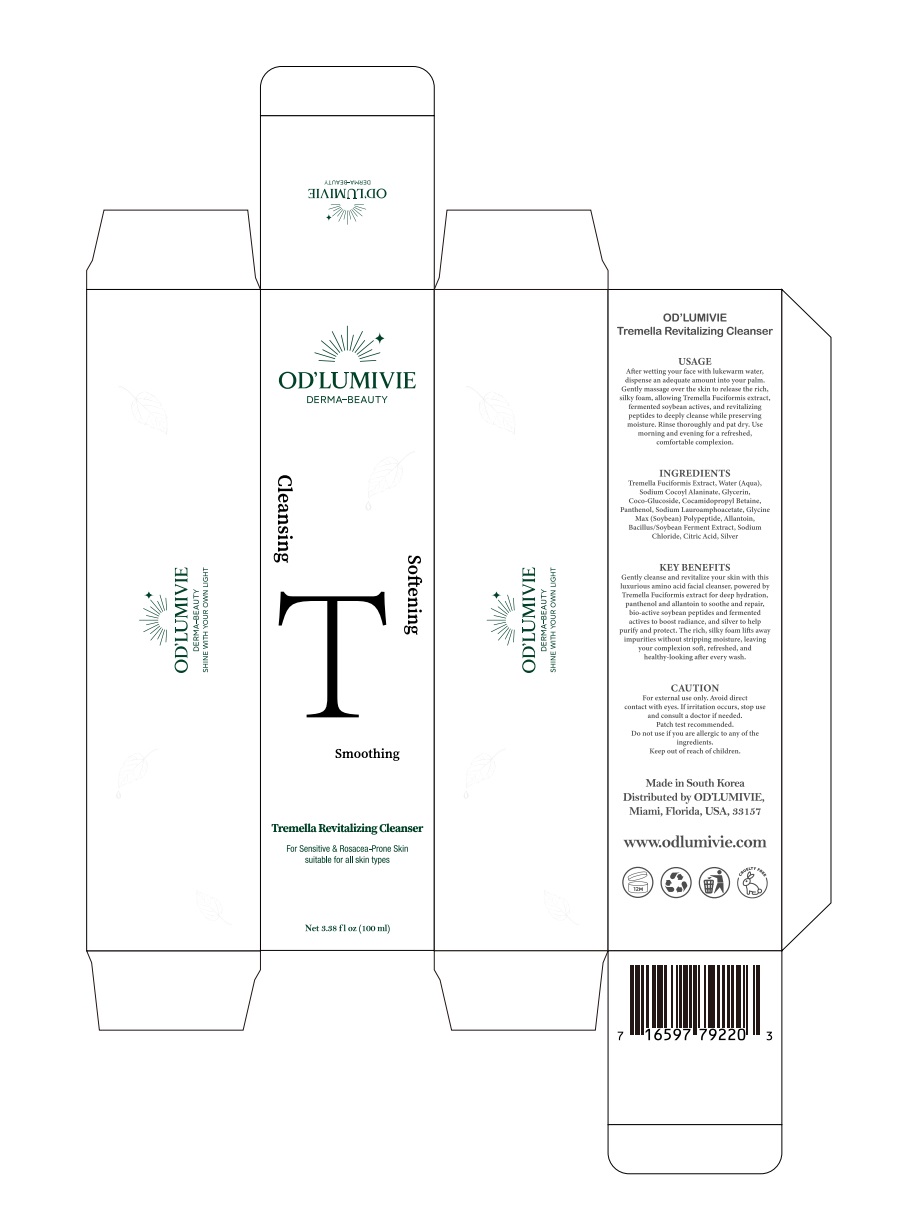 DRUG LABEL: ODLUMIVIE Tremella Revitalizing Cleanser
NDC: 87036-026 | Form: LIQUID
Manufacturer: OD’LUMIVIE
Category: otc | Type: HUMAN OTC DRUG LABEL
Date: 20251111

ACTIVE INGREDIENTS: TREMELLA FUCIFORMIS WHOLE 1 g/100 mL
INACTIVE INGREDIENTS: ALLANTOIN; SODIUM CHLORIDE; WATER; GLYCINE MAX (SOYBEAN) OIL; CITRIC ACID; SODIUM LAUROAMPHOACETATE; COCAMIDOPROPYL BETAINE; SODIUM COCOYL ALANINATE; GLYCERIN; COCO-GLUCOSIDE; PANTHENOL

ACTIVE INGREDIENT

INACTIVE INGREDIENT

INGREDIENTS
Tremella Fuciformis Extract, Water (Aqua),Sodium Cocoyl Alaninate, Glycerin,Coco-Glucoside, Cocamidopropyl Betaine,Panthenol, Sodium Lauroamphoacetate, GlycineMax (Soybean) Polypeptide, Allantoin,Bacillus/Soybean Ferment Extract, SodiumChloride, Citric Acid, Silver

PURPOSE

KEY BENEFITSGently cleanse and revitalize your skin with thisluxurious amino acid facial cleanser, powered byTremella Fuciformis extract for deep hydration,panthenol and allantoin to soothe and repair,bio-active soybean peptides and fermentedactives to boost radiance, and silver to helppurify and protect. The rich, silky foam lifts awayimpurities without stripping moisture, leavingyour complexion soft, refreshed, andhealthy-looking after every wash.

WARNINGS

CAUTION
For external use only, Avoid direct contact with eyes. Ifirritation occurs, stop useand consult a doctor if needed. Patch test recommended, Do not use if you areallergic to any of the ingredients. Keep out of reach of children.

DO NOT USE

CAUTION
For external use only, Avoid direct contact with eyes. Ifirritation occurs, stop useand consult a doctor if needed. Patch test recommended, Do not use if you areallergic to any of the ingredients. Keep out of reach of children.

KEEP OUT OF REACH OF CHILDREN

CAUTION
For external use only, Avoid direct contact with eyes. Ifirritation occurs, stop useand consult a doctor if needed. Patch test recommended, Do not use if you areallergic to any of the ingredients. Keep out of reach of children.

STOP USE

CAUTION
For external use only, Avoid direct contact with eyes. Ifirritation occurs, stop useand consult a doctor if needed. Patch test recommended, Do not use if you areallergic to any of the ingredients. Keep out of reach of children.

USAGE
After wetting your face with lukewarm water,dispense an adequate amount into your palm.Gently massage over the skin to release the rich,silky foam, allowing Tremella Fuciformis extract,fermented soybean actives, and revitalizingpeptides to deeply cleanse while preservingmoisture. Rinse thoroughly and pat dry. Usemorning and evening for a refreshed,comfortable complexion.

WHEN USING

USAGE
After wetting your face with lukewarm water,dispense an adequate amount into your palm.Gently massage over the skin to release the rich,silky foam, allowing Tremella Fuciformis extract,fermented soybean actives, and revitalizingpeptides to deeply cleanse while preservingmoisture. Rinse thoroughly and pat dry. Usemorning and evening for a refreshed,comfortable complexion.

DOSAGE AND ADMINISTRATION

USAGE
After wetting your face with lukewarm water,dispense an adequate amount into your palm.Gently massage over the skin to release the rich,silky foam, allowing Tremella Fuciformis extract,fermented soybean actives, and revitalizingpeptides to deeply cleanse while preservingmoisture. Rinse thoroughly and pat dry. Usemorning and evening for a refreshed,comfortable complexion.

PACKAGE LABEL

USAGE
ODLUMIVIE
DERMA-BEAUTY
Cleansing
Softening
IIAIWATGO
LH9I NMO HNOX HLIM 3NIHS人InV38-VW830
After wetting your face with lukewarm waterdispense an adequate amount into your palm.Gently massage over the skin to release the richsilky foam,allowing Tremella Fuciformis extract,fermented soybean actives,and revitalizingpeptides to deeply cleanse while preservingmoisture,Rinse thoroughly and pat dry.Usemorning and evening for a refreshed,
comfortable complexion.
INGREDIENTSTremella Fuciformis Extract,Water(Aqua)Sodium CocoylAlaninate,Glycerin,Coco-Glucoside,Cocamidopropyl Betaine,Panthenol,Sodium Lauroamphoacetate,GlycineMax(Soybean)Polypeptide,Allantoin,Bacillus/Soybean Ferment Extract, SodiumChloride, Citric Acid, Silver
KEY BENEFITS
Gently cleanse and revitalize your skin with thisluxurious amino acid facial cleanser,powered byTremella Fuciformis extract for deep hydration,panthenol and allantoin to soothe and repair,bio-active soybean peptides and fermentedactives to boost radiance, and silver to helppurify and protect. The rich, silky foam lifts awayimpurities without stripping moisture, leavingyour complexion soft,refreshed, andhealthy-looking after every wash.
CAUTIONFor external use only. Avoid directcontact with eyes.Ifirritation occurs,stop useand consult a doctor ifneeded.Patch test recommended.
Do not use ifyou are allergic to any ofthe
Smoothing
ingredients.
Keep out ofreach ofchildren.